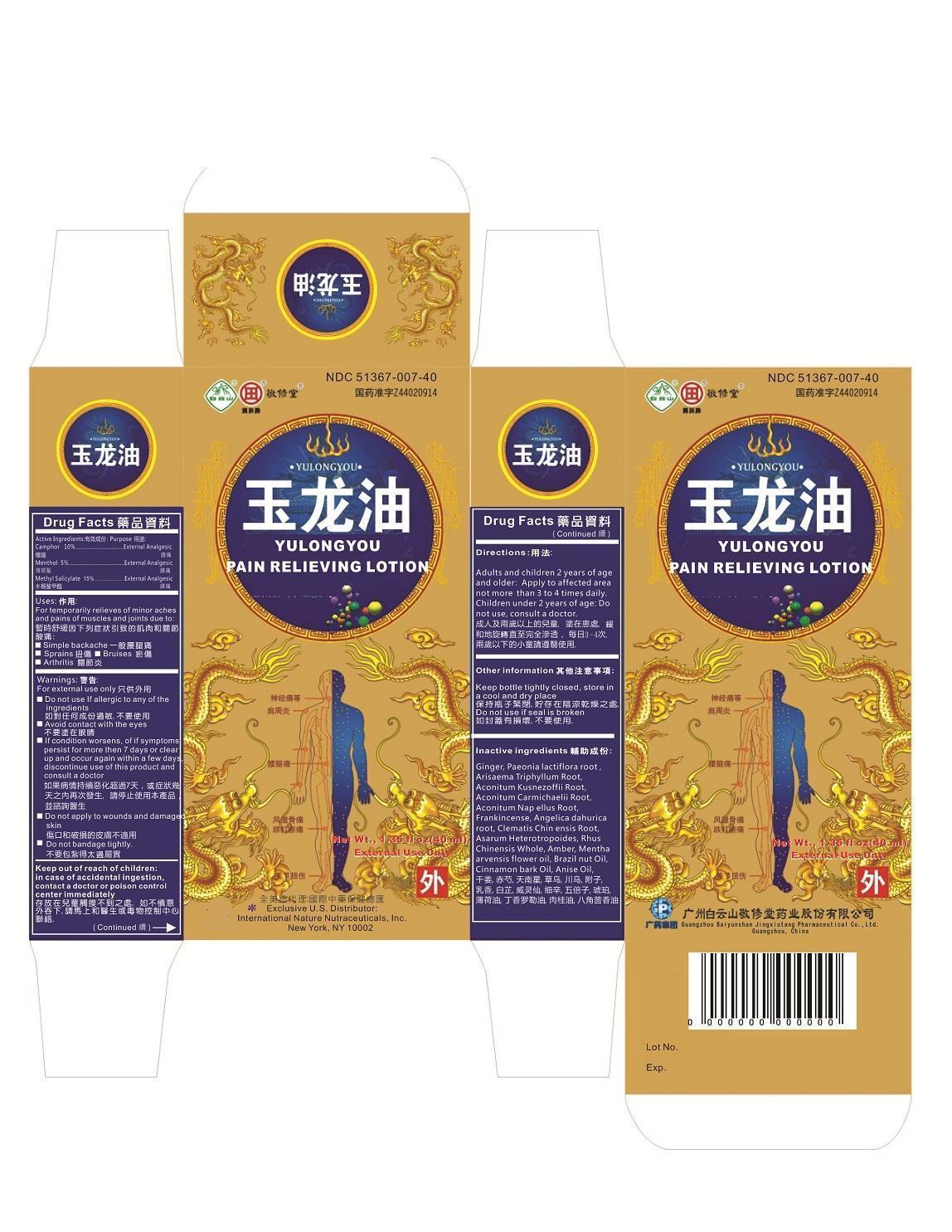 DRUG LABEL: Yu Long You Pain Relieving
NDC: 51367-007 | Form: LOTION
Manufacturer: International Nature Nutraceuticals
Category: otc | Type: HUMAN OTC DRUG LABEL
Date: 20191226

ACTIVE INGREDIENTS: CAMPHOR (NATURAL) 3.97 g/1 1; MENTHOL 1.78 g/1 1; METHYL SALICYLATE 7.04 g/1 1
INACTIVE INGREDIENTS: GINGER; PAEONIA LACTIFLORA ROOT; ARISAEMA TRIPHYLLUM ROOT; ACONITUM KUSNEZOFFII ROOT; ACONITUM CARMICHAELII ROOT; ACONITUM NAPELLUS ROOT; FRANKINCENSE; ANGELICA DAHURICA ROOT; CLEMATIS CHINENSIS ROOT; ASARUM HETEROTROPOIDES; RHUS CHINENSIS WHOLE; AMBER; MENTHA ARVENSIS FLOWER OIL; BRAZIL NUT OIL; CINNAMON BARK OIL; ANISE OIL

Drug Facts

Active Ingredients:

Camphor 10%

Menthol 5%

Methyl Salicylate 15%

Uses

For temporarily relieves of minor aches and pains of muscles and joints due to:

- Simple backache
- sprains
- bruises
- arthritis

Warnings:

For External Use only

Do not use if allergic to any of the ingredients

Avoid contact with the eyes

If condition worsens, of if sympotoms persist for more then 7 days or clear up and occur again within a few days, discontinue use of this product and consult a doctor

Do not apply to wounds and damaged skin

Do not bandage tightly

Keep out of reach of children

In case of accidental ingestion, contact a doctor or poison control center immediately

Directions

Adults and children 2 years of age and older: Apply to affected area not more than 3 to 4 times daily

Children under 2 years of age: Do not use, consult a doctor

Other information

Keep bottle tightly closed, store in a cool and dry place

Do not use if seal is broken

Inactive ingredients

干姜. Ginger 赤芍。 Paeonia lactiflora root. 天南星 Arisaema Triphyllum Root 草乌 Aconitum Kusnezoffii Root 川乌 Aconitum Carmichaelii Root 附子 Aconitum Napellus Root #乳香。 Frankincense 白芷。 . Angelica dahurica root. 威灵仙 Clematis Chinensis Root 细辛 Asarum Heterotropoides 五倍子 Rhus Chinensis Whole 琥珀 Amber. 薄荷油. . Mentha arvensis flower oil. 丁香罗勒油 Brazil nut Oil. 肉桂油 Cinnamon bark Oil 八角茴香油 Anise Oil.